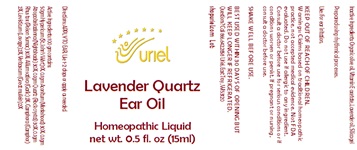 DRUG LABEL: Lavender Quartz Ear Oil
NDC: 48951-6021 | Form: LIQUID
Manufacturer: Uriel Pharmacy Inc.
Category: homeopathic | Type: HUMAN OTC DRUG LABEL
Date: 20251117

ACTIVE INGREDIENTS: ST. JOHN'S WORT 1 [hp_X]/1 mL; ACONITUM NAPELLUS 30 [hp_X]/1 mL; ATROPA BELLADONNA 30 [hp_X]/1 mL; SILICON DIOXIDE 30 [hp_X]/1 mL; TOXICODENDRON PUBESCENS LEAF 30 [hp_X]/1 mL; GARLIC 2 [hp_X]/1 mL; CAMPHOR (NATURAL) 2 [hp_X]/1 mL; LEVISTICUM OFFICINALE ROOT 2 [hp_X]/1 mL; VERBASCUM DENSIFLORUM LEAF 2 [hp_X]/1 mL
INACTIVE INGREDIENTS: OLIVE OIL; .ALPHA.-TOCOPHEROL ACETATE; LAVENDER OIL

Lavender Quartz Ear Oil

INDICATIONS AND USAGE

Directions: Apply to ear

DOSAGE AND ADMINISTRATION

Use 1-2 drops or apply as needed.

ACTIVE INGREDIENT

Active Ingredients: 100 gm contains: 50gm Hypericum (St. John’s Wort) 1X, 0.1gm Aconitum (Monkshood) 30X, 0.1gm Atropa belladonna (Nightshade) 30X, 0.1gm Quartz (Rock crystal) 30X, 0.1gm Rhus tox (Poison Sumac) 30X; Allium sativa (Garlic) 2X, Camphora (Camphor) 2X, Levisticum (Lovage) 2X, Verbascum (Great mullein) 2X

INACTIVE INGREDIENT

Inactive Ingredients: Organic olive oil, Vitamin E acetate, Lavender oil, Silica gel

Prepared using rhythmical processes.

PURPOSE

Use: For ear irritation

KEEP OUT OF REACH OF CHILDREN.

WARNINGS

Warnings: Claims based on traditional homeopathic practice, not accepted medical evidence. Not FDA evaluated. Do not use if allergic to any ingredient. Consult a doctor before use for serious conditions or if conditions worsen or persist. If pregnant or nursing, consult a doctor before use.

SHAKE WELL BEFORE USE.

BEST USED WITHIN 30 DAYS OF OPENING BUT WILL KEEP LONGER IF REFRIGERATED.

Questions? Call 866.642.2858
Uriel, East Troy, WI 53120
shopuriel.com Lot: